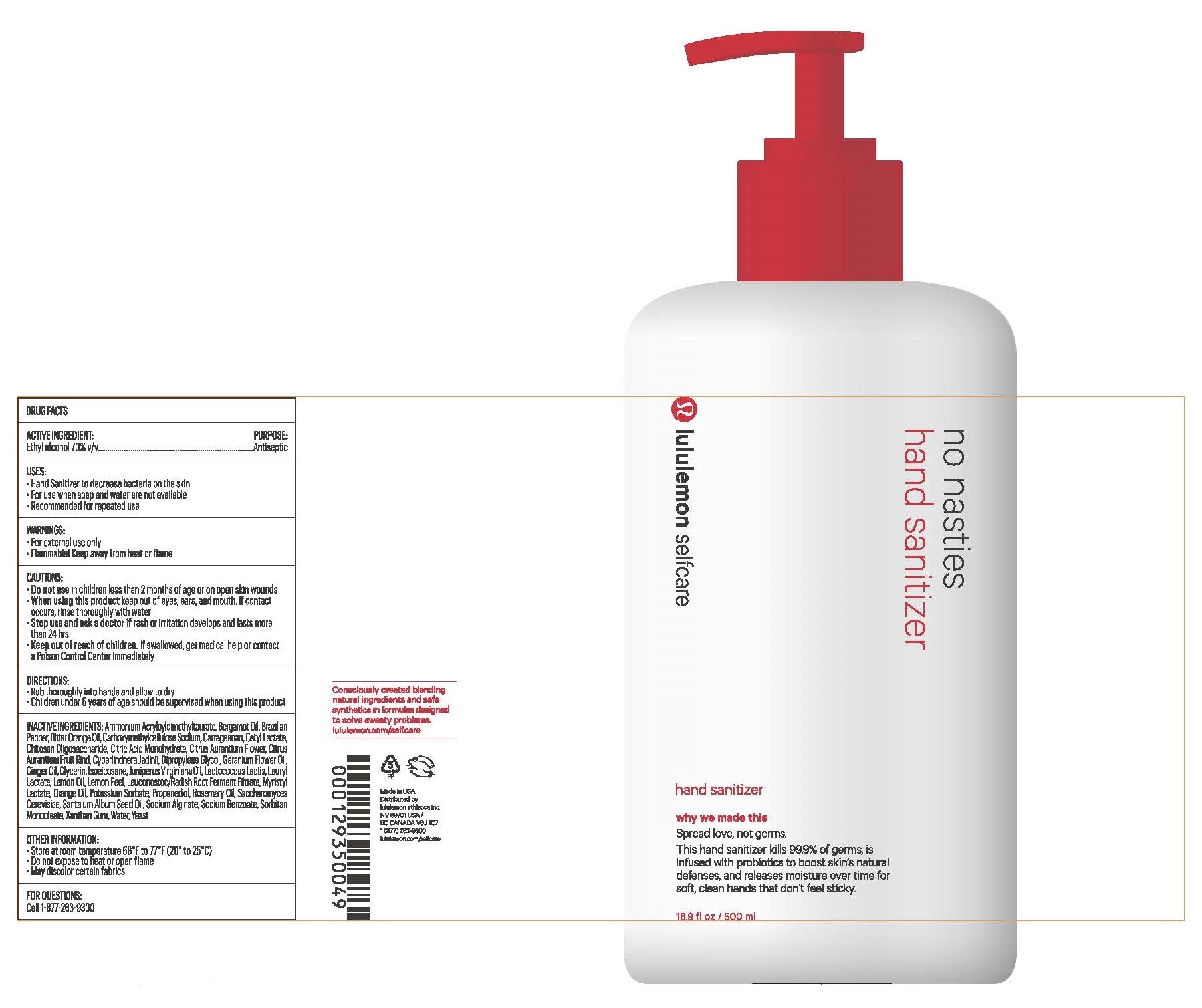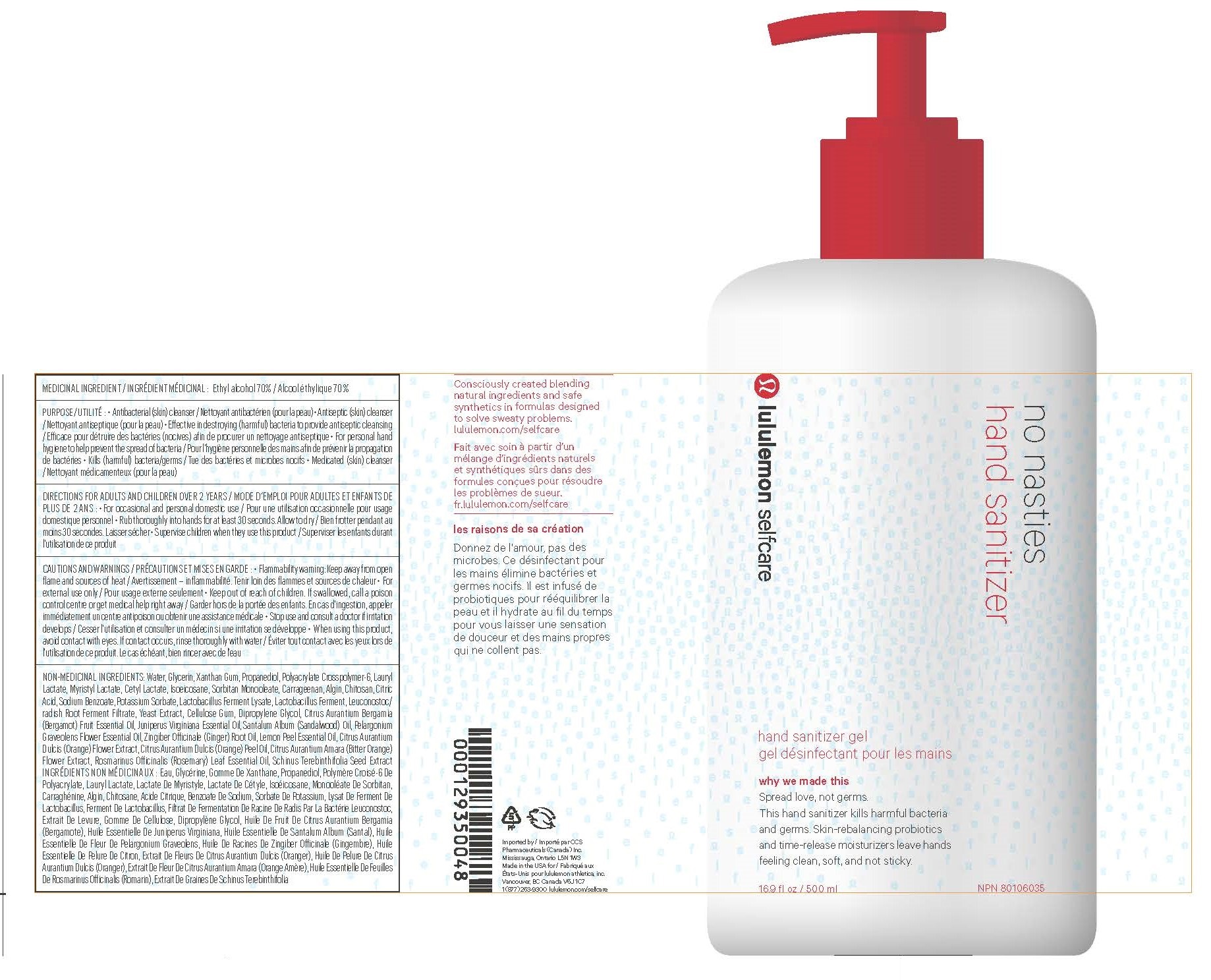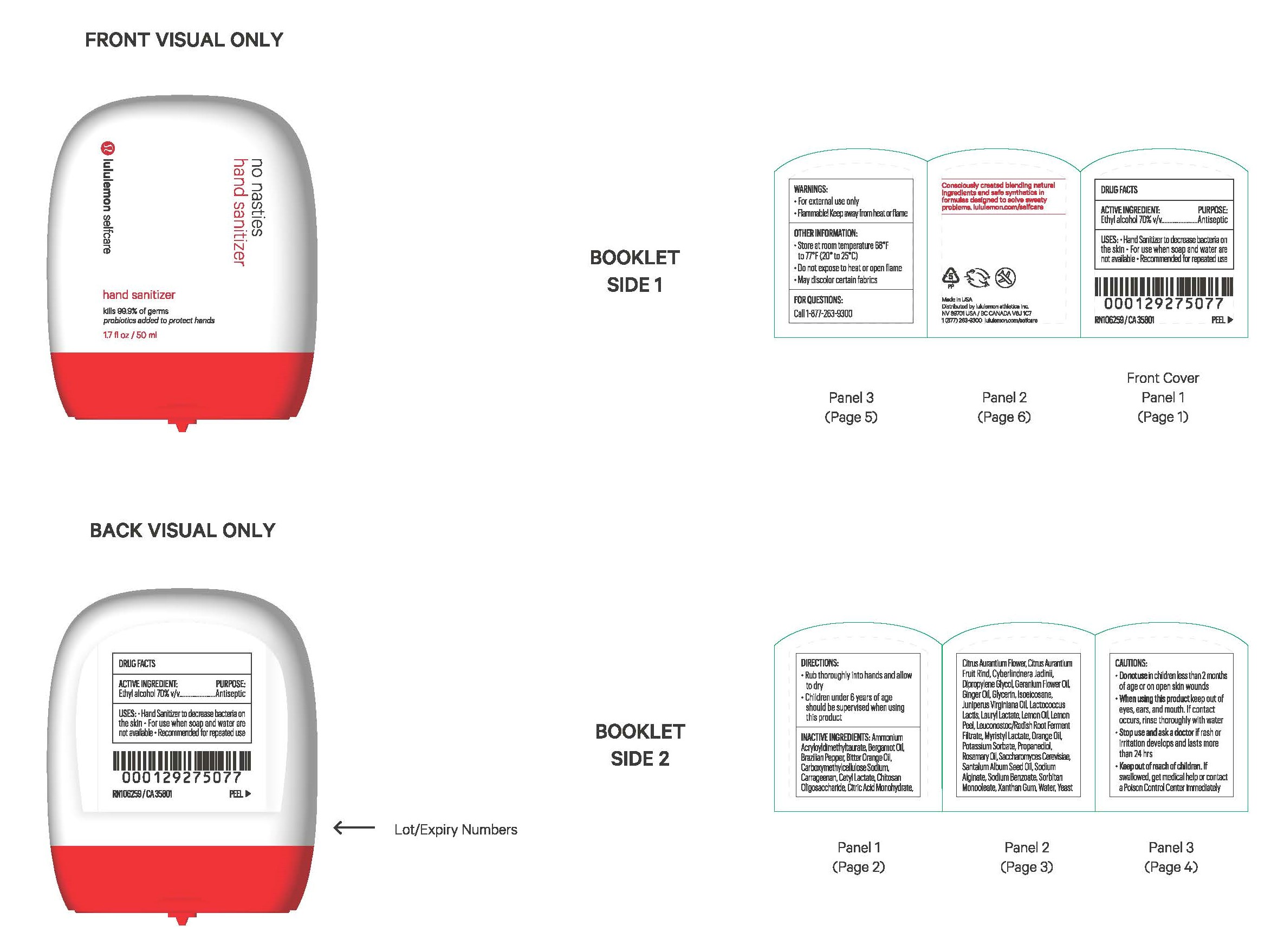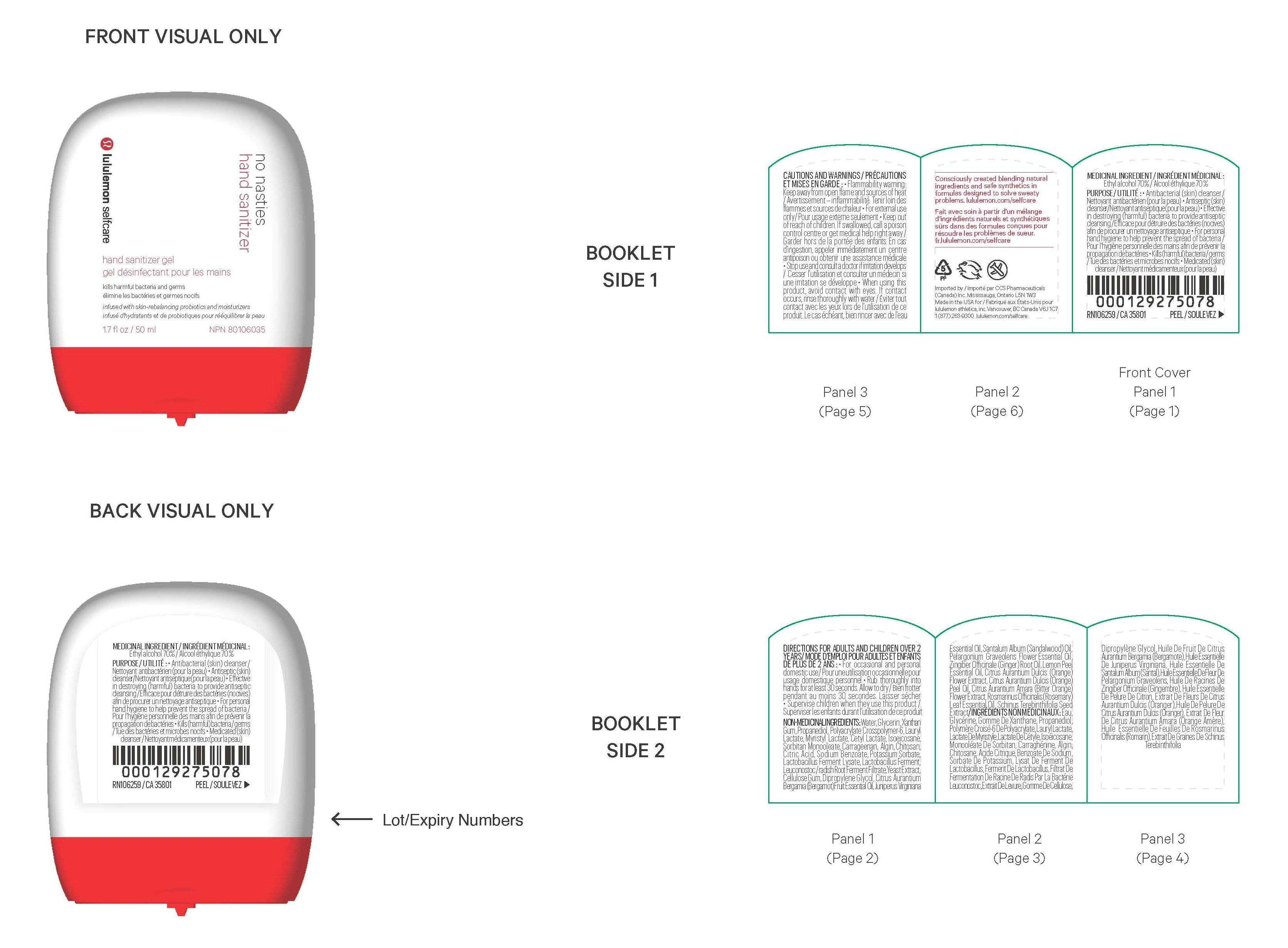 DRUG LABEL: Lululemon Selfcare No Nasties Hand Sanitizer
NDC: 52261-8700 | Form: SOLUTION
Manufacturer: Cosco International, Inc.
Category: otc | Type: HUMAN OTC DRUG LABEL
Date: 20210429

ACTIVE INGREDIENTS: ALCOHOL 70 L/100 L
INACTIVE INGREDIENTS: AMMONIUM ACRYLOYLDIMETHYLTAURATE; BERGAMOT OIL; BRAZILIAN PEPPER; BITTER ORANGE OIL; CARBOXYMETHYLCELLULOSE SODIUM; CARRAGEENAN; CETYL LACTATE; CHITOSAN OLIGOSACCHARIDE; CITRIC ACID MONOHYDRATE; CITRUS AURANTIUM FLOWER; CITRUS AURANTIUM FRUIT RIND; DIPROPYLENE GLYCOL; GERANIUM OIL, ALGERIAN TYPE; GINGER OIL; GLYCERIN; ISOEICOSANE; JUNIPERUS VIRGINIANA OIL; LACTOCOCCUS LACTIS; LAURYL ACETATE; LEMON OIL; LEMON PEEL; LEUCONOSTOC/RADISH ROOT FERMENT FILTRATE; MYRISTYL LACTATE; ORANGE OIL; CYBERLINDNERA JADINII; POTASSIUM SORBATE; PROPANEDIOL; ROSEMARY OIL; SACCHAROMYCES CEREVISIAE; SANTALUM ALBUM SEED OIL; SODIUM ALGINATE; SODIUM BENZOATE; SORBITAN MONOOLEATE; XANTHAN GUM; WATER; YEAST

ACTIVE INGREDIENT:

Ethyl Alcohol 70% v/v.................Purpose: Antiseptic

PURPOSE:

Antiseptic

USES:

- Hand Sanitizer to decrease bacteria on the skin
- For use when soap and water are not available
- Recommended for repeated use

WARNINGS:

- For external use only
- Flammable! Keep away from heat or flame

CAUTIONS:

- Do not use in children less than 2 months of age or on open skin wounds

- When using this product keep out of eyes, ears, and mouth. If contact occurs, rinse thoroughly with water.

- Stop use and ask a doctor if rash or irratation develops and last more than 24 hours.

- Keep out of reach of children. If swallowed, get medical help or contact a Poison Control Center immediately.

DIRECTIONS:

- Rub thoroughly into hands and allow to dry
- Children under 6 years of age should be supervised when using this product

INACTIVE INGREDIENTS:

Ammonium Acryloyldimethyltaurate, Bergamot Oil, Brazilian Pepper, Bitter Orange Oil,
Carboxymethylcellulose Sodium, Carrageenan, Cetyl Lactate, Chitosan Oligosaccharide, Citric Acid
Monohydrate, Citrus Aurantium Flower, Citrus Aurantium Fruit Rind, Cyberlindnera Jadinii, Dipropylene
Glycol, Geranium Flower Oil, Ginger Oil, Glycerin, Isoeicosane, Juniperus Virginiana Oil, Lactococcus
Lactis, Lauryl Lactate, Lemon Oil, Lemon Peel, Leuconostoc/Radish Root Ferment Filtrate, Myristyl
Lactate, Orange Oil, Potassium Sorbate, Propanediol, Rosemary Oil, Saccharomyces Cerevisiae, Santalum
Album Seed Oil, Sodium Alginate, Sodium Benzoate, Sorbitan Monooleate, Xanthan Gum, Water, Yeast

OTHER INFORMATION:

- Store at room temperature 68° F to 77° F (20° to 25° C)
- Do not expose to heat or open flame
- May discolor certain fabrics

FOR QUESTIONS:

Call 1-877-263-9300